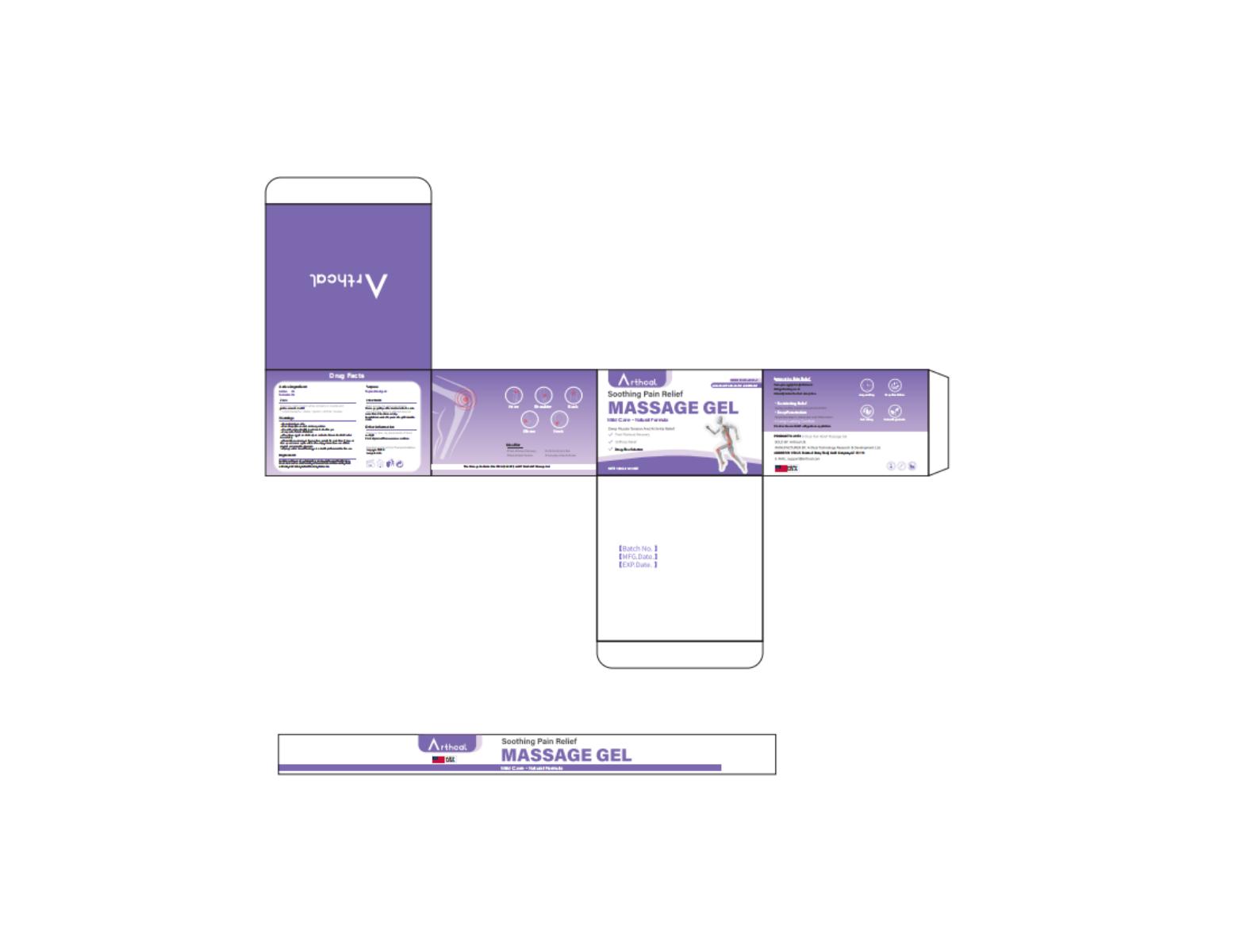 DRUG LABEL: Arthcal  SOOTHING PAIN RELIEF MASSAGE
NDC: 85212-0039 | Form: GEL
Manufacturer: Beijing JUNGE Technology Co., Ltd.
Category: otc | Type: HUMAN OTC DRUG LABEL
Date: 20250806

ACTIVE INGREDIENTS: EMU OIL 1 g/100 g; TURMERIC 1 g/100 g; ARNICA MONTANA 2 g/100 g; MENTHOL 3 g/100 g
INACTIVE INGREDIENTS: CINNAMON OIL 0.5 g/100 g; AQUA 44.5 g/100 g; GLYCERIN 1 g/100 g; ISOPROPYL ALCOHOL 16.2 g/100 g; ALCOHOL 30 g/100 g; EUCALYPTUS OIL 0.8 g/100 g

DOSAGE AND ADMINISTRATION

100g(3.53oz)

ACTIVE INGREDIENT

EMU OIL
MENTHOL

ARNICA MONTANA

TURMERIC

INACTIVE INGREDIENT

EUCALYPTUS OIL
CINNAMON OIL
GLYCERIN
ALCOHOL
ISOPROPYLAL COHOL
AQUA

INDICATIONS AND USAGE

Wash and dry the area to be applied.
Massage gently until absorbed into the skin.
Adult dosage: apply to affected area not more than 3 to 4 times daily.
For children under 14 years of age: Consult a doct

PURPOSE

Topical Analgesic

Keep out of reach of children

WARNINGS

For external use only
Do not apply to wounds or damaged skin
Do not bandage tightly .Avoid contact with eyes
Keep out of reach of children
If swallowed, get medical help or contact a Poison Control Center immediately.
lf condition worsens, or if symptoms persist for more than 7 days or clear up and occur again within afew days, discontinue use of this product and consult a physician
lf pregnant or breast feeding, ask a health professional before use

OTHER SAFETY INFORMATION

Store in a clean, dry placeoulside of direct sunlight
Protect product fromexcessive moisture